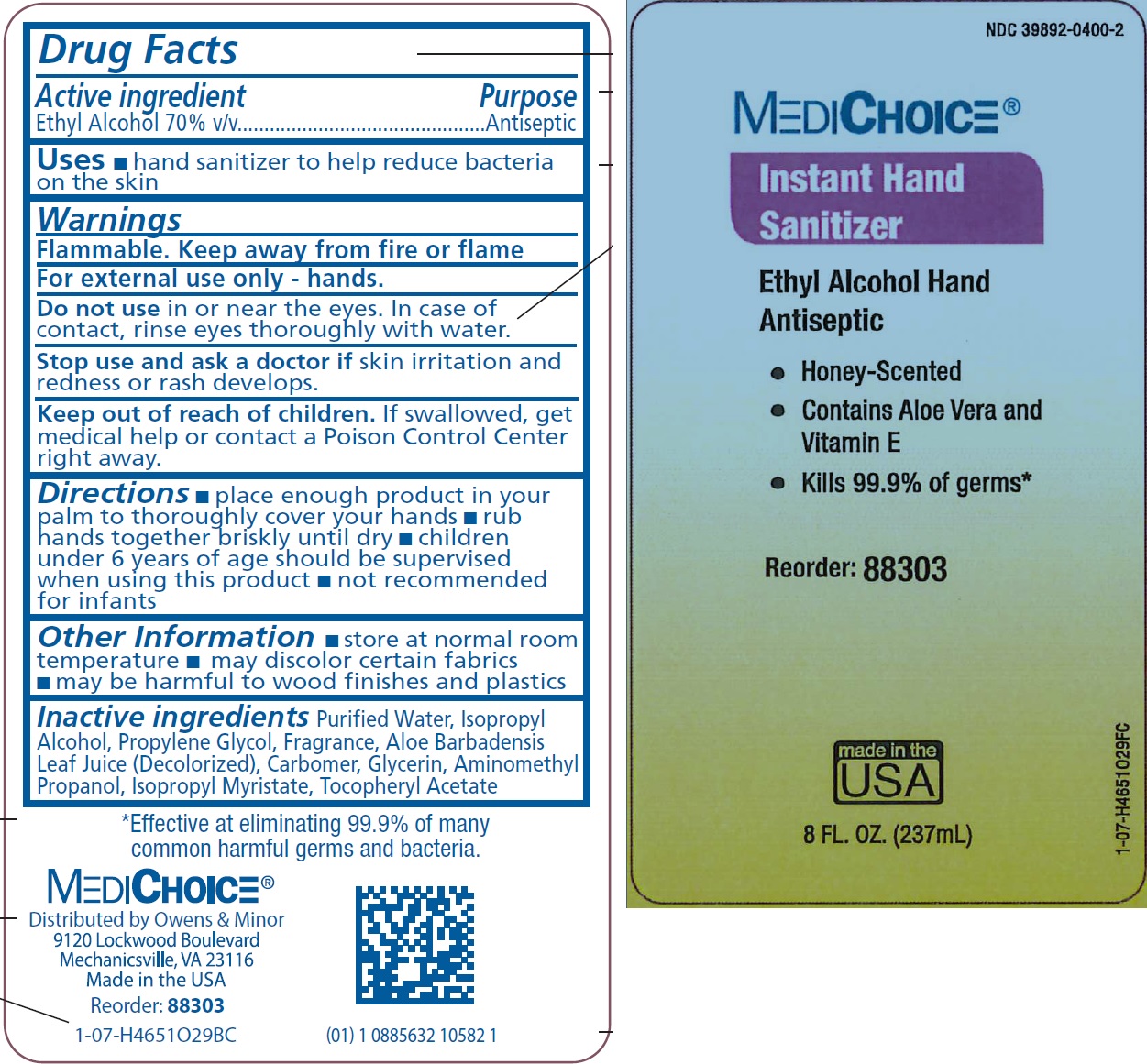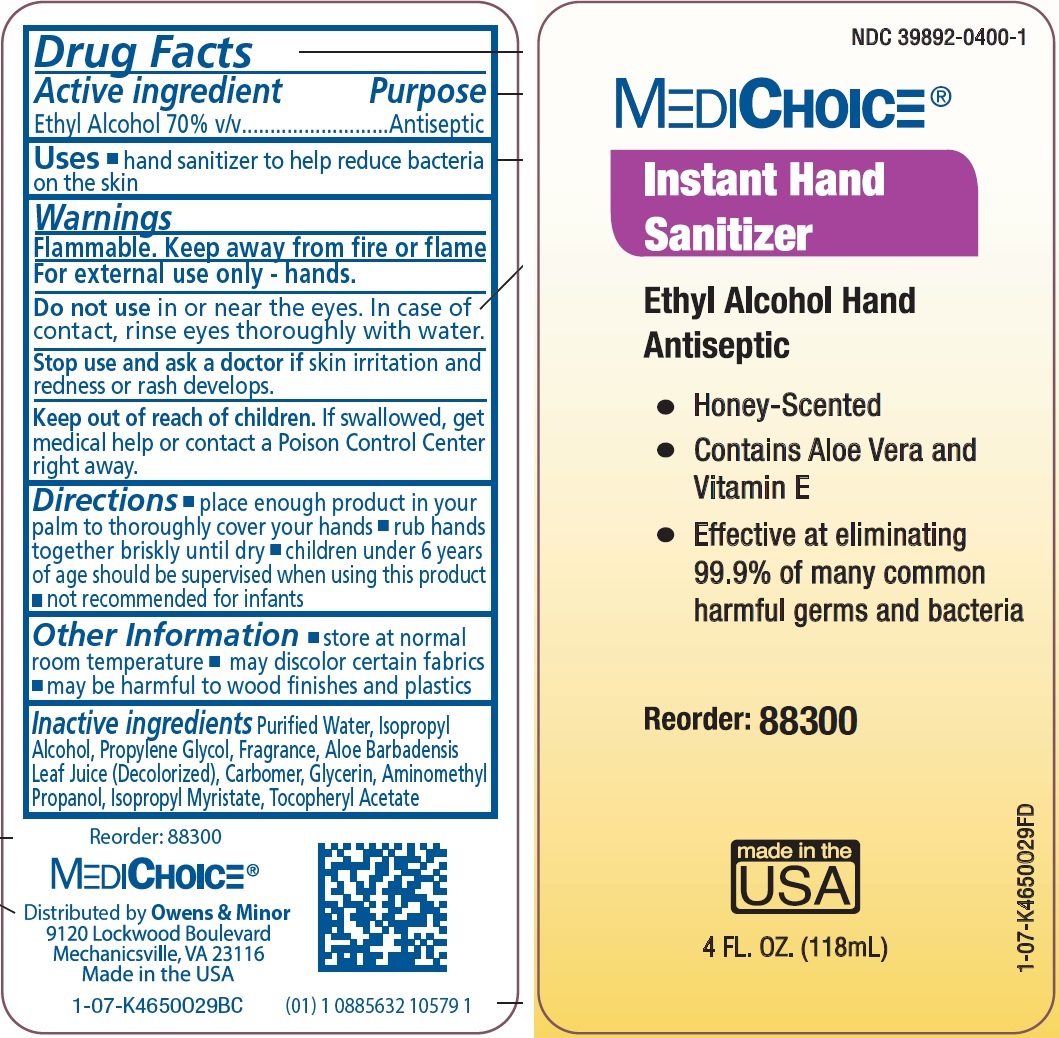 DRUG LABEL: 
                  MediChoice Instant Hand Sanitizer

                
                  


NDC: 39892-0400 | Form: GEL
Manufacturer: O&M HALYARD, INC.
Category: otc | Type: HUMAN OTC DRUG LABEL
Date: 20251008

ACTIVE INGREDIENTS: ALCOHOL 700 mg/1 mL
INACTIVE INGREDIENTS: WATER; ISOPROPYL ALCOHOL; PROPYLENE GLYCOL; ALOE VERA LEAF; CARBOXYPOLYMETHYLENE; GLYCERIN; AMINOMETHYLPROPANOL; ISOPROPYL MYRISTATE

MediChoice Instant Hand Sanitizer (Honey-scented)

Active ingredient

Ethyl Alcohol 70% v/v

Purpose

Antiseptic

Uses

- hand sanitizer to help reduce bacteria on the skin

Warnings

Flammable. Keep away from fire or flame

For external use only - hands.

Do not use

in or near the eyes. In case of contact, rinse eyes thoroughly with water

Stop use and ask a doctor

if skin irritation and redness or rash develops.

Keep out of reach of children.

If swallowed, get medical help or contact a Poison Control Center right away.

Directions

- place enough product in your palm to thoroughly cover your hands
- rub hands together briskly until dry
- children under 6 years of age should be supervised when using this product
- not recommended for infants

Other Information

- store at normal room temperature
- may discolor certain fabrics
- may be harmful to wood finishes and plastics

Inactive ingredients

Purified Water, Isopropyl Alcohol, Propylene Glycol, Fragrance, Aloe Barbadensis Leaf Juice (Decolorized), Carbomer, Glycerin, Aminomethyl Propanol, Isopropyl Myristate, Tocopheryl Acetate